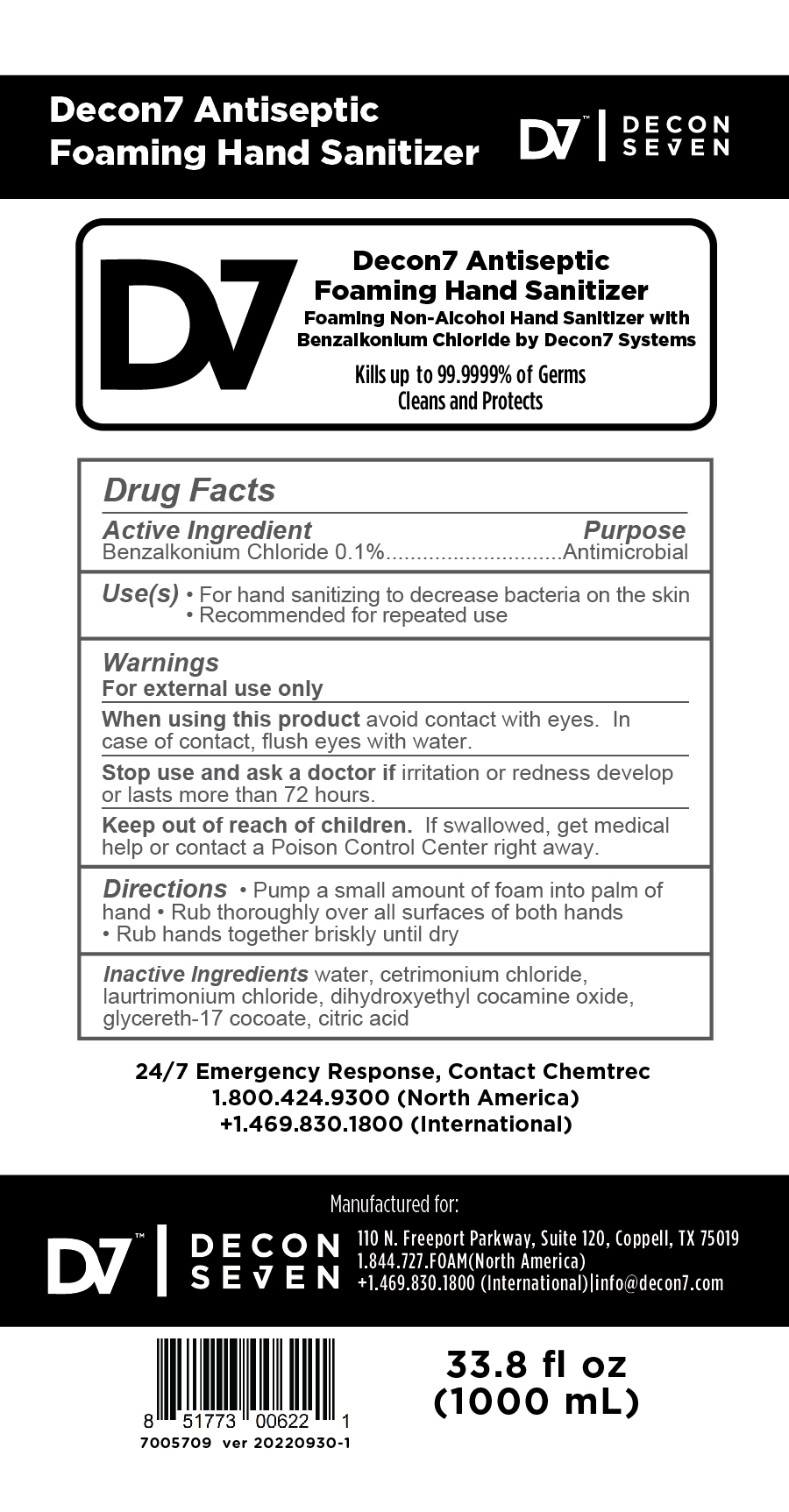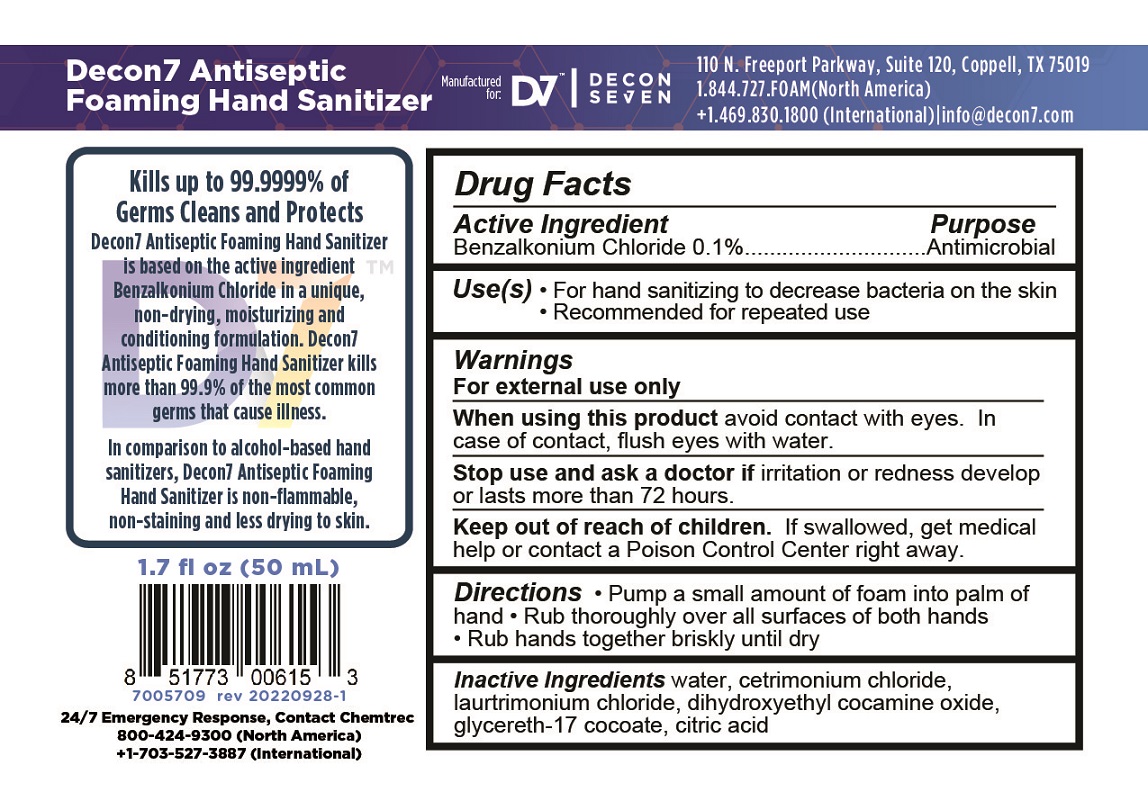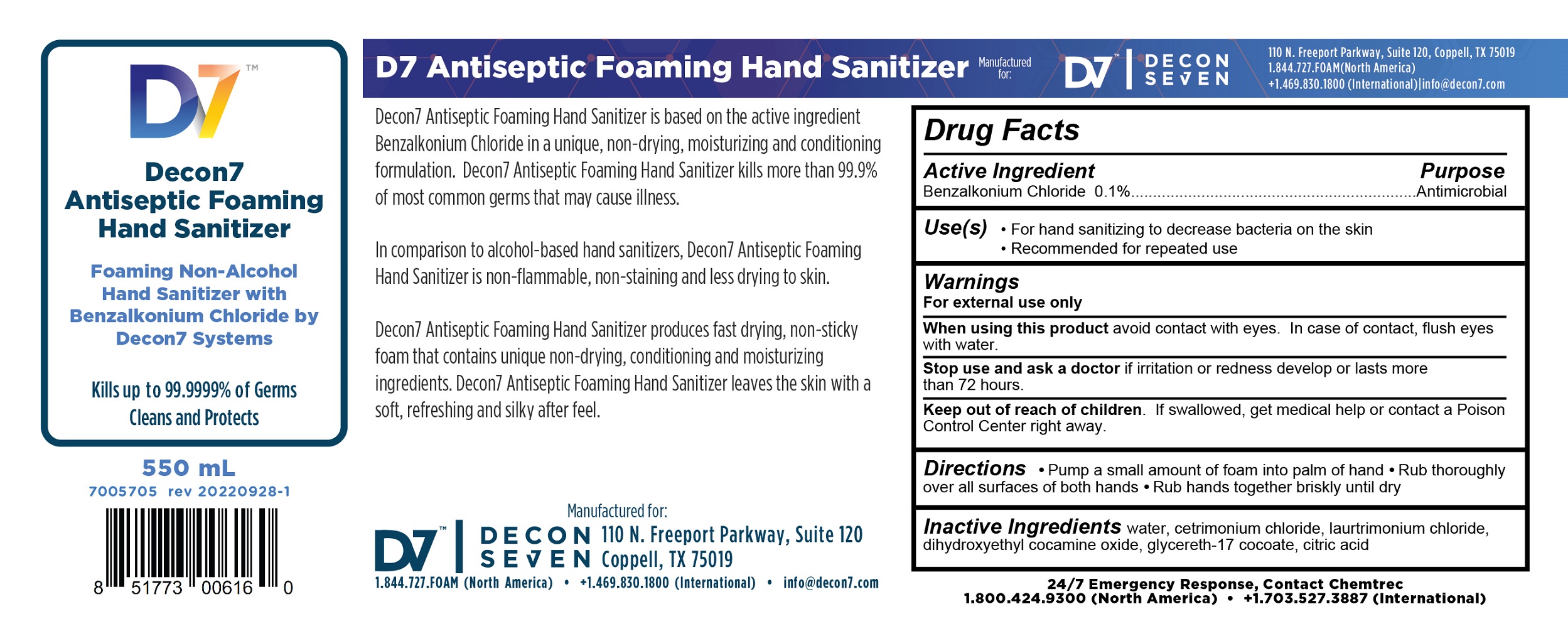 DRUG LABEL: Decon7 Antiseptic Foaming Hand Sanitizer
NDC: 78245-201 | Form: LIQUID
Manufacturer: Decon7 Systems, LLC
Category: otc | Type: HUMAN OTC DRUG LABEL
Date: 20231016

ACTIVE INGREDIENTS: BENZALKONIUM CHLORIDE 1 mg/1 mL
INACTIVE INGREDIENTS: DIHYDROXYETHYL COCAMINE OXIDE; CITRIC ACID MONOHYDRATE; WATER; LAURTRIMONIUM CHLORIDE; GLYCERETH-17 COCOATE; CETRIMONIUM CHLORIDE

Decon7 Antiseptic Foaming Hand Sanitizer

Active Ingredient

Benzalkonium Chloride 0.1%

Purpose

Antimicrobial

Uses

- For hand sanitizing to decrease bacteria on the skin
- Recommended for repeated use

Warnings

For external use only

When using this product avoid contact with eyes. In case of eye contact, flush eyes thoroughly with water.

Stop use and ask a doctor if irritation or redness develop or last more than 72 hours.

Keep out of reach of children. If swallowed, get medical help or contact a Poison Control Center right away.

Directions

- Pump a small amount of foam into palm of hand
- Rub thoroughly over all surfaces of both hands
- Rub hands together briskly until dry

Inactive Ingredients

Water, cetrimonium chloride, laurtrimonium chloride, dihydroxyethyl cocamine oxide, glycereth-17 cocoate, citric acid

PACKAGE LABEL

Decon7 Antiseptic Foaming Hand Sanitizer
Manufactured for: D7™ DECON SEVEN

110 North Freeport Parkway, Suite 120, Coppell, TX 75019

1.844.727.FOAM (North America)

+1.469.830.1800 (International) | info@decon7.com

1.7 fl oz (50 mL)

24/7 Emergency Response, Contact Chemtrec

800-424-9300 (North America)

+1-703-527-3887 (International)